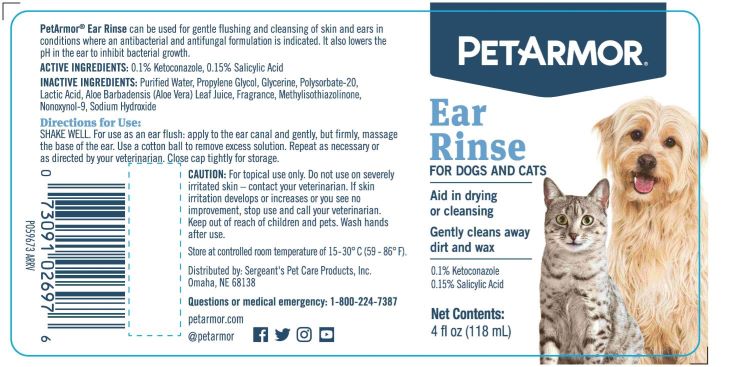 DRUG LABEL: 0.1% Ketoconazole, 0.15% Salicylic Acid
NDC: 21091-269 | Form: SOLUTION, GEL FORMING / DROPS
Manufacturer: Sergeant's Pet Care Products LLC
Category: animal | Type: OTC ANIMAL DRUG LABEL
Date: 20240419

ACTIVE INGREDIENTS: KETOCONAZOLE 0.1 1/1 1; SALICYLIC ACID 0.15 1/1 1
INACTIVE INGREDIENTS: WATER; PROPYLENE GLYCOL; GLYCERIN; POLYSORBATE 20; LACTIC ACID; ALOE VERA LEAF; METHYLISOTHIAZOLINONE; NONOXYNOL-9; SODIUM HYDROXIDE

PetArmor Ear Rinse for dogs and cats

PURPOSE

PetArmor® Ear Rinse

For Dogs and Cats

Aid in drying or cleansing

Gently cleans away dirt and was

PetArmor® Ear Rinse can be used for gentle flushing and cleansing of skin and ears in conditions where an antibacterial and antifungal formulation is indicated. It also lowers the pH in the ear to inhibit bacterial growth.

ACTIVE INGREDIENTS:

0.1% Ketoconazole, 0.15% Salicylic Acid

INACTIVE INGREDIENTS:

Purified Water, Propylene Glycol, Glycerin, Polysorbate 20, Lactic Acid, Ale Barbadensis (Aloe Vera) Leaf Juice, Methylisothiazolinone, Nonoxynol-9, Sodium Hydroxide

Directions for Use:

SHAKE WELL. For use as an ear flush: apply to the ear canal and gently, but firmly, massage the base of the ear. Use a cotton ball to remove excess solution. Repeat as necessary or as directed by your veterinarian. Close cap tightly for storage.

CAUTION:

For topical use only. Do not use on severely irritated skin – contact your veterinarian. If skin irritation develops or increases or you see no
improvement, stop use and call your veterinarian. Keep out of reach of children and pets. Wash hands after use.

STORAGE AND HANDLING

Store at controlled room temperature of 15 - 30° C (59 - 86° F).

Questions or medical emergency: 1-800-224-7387